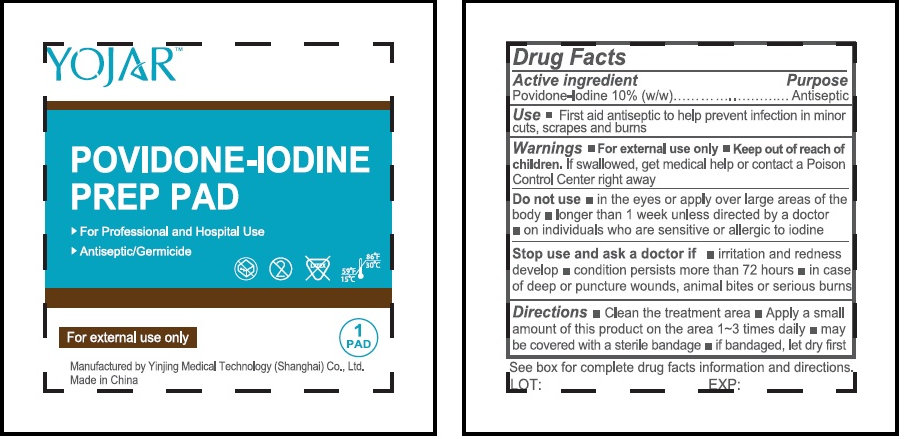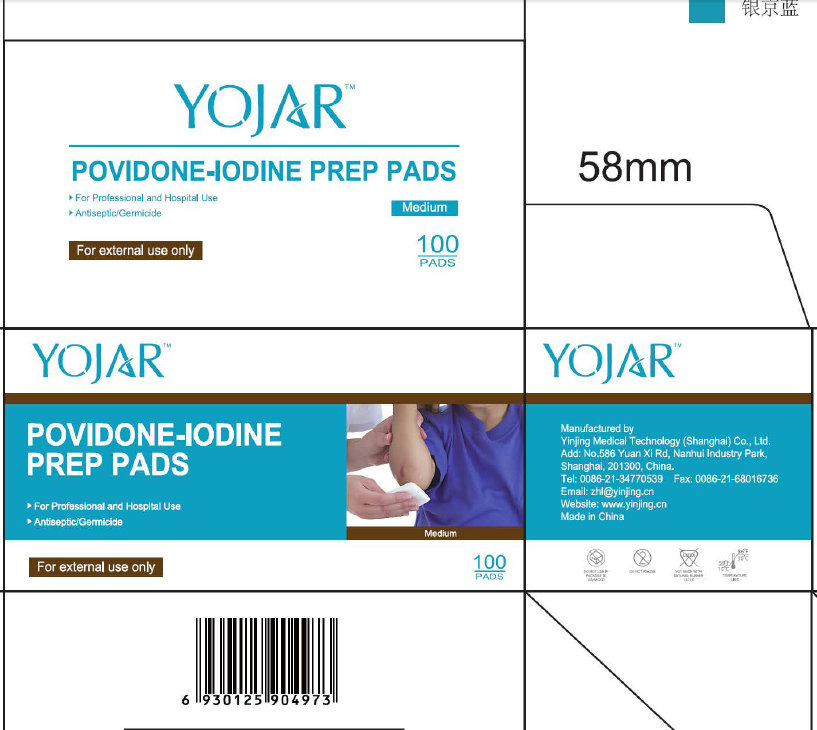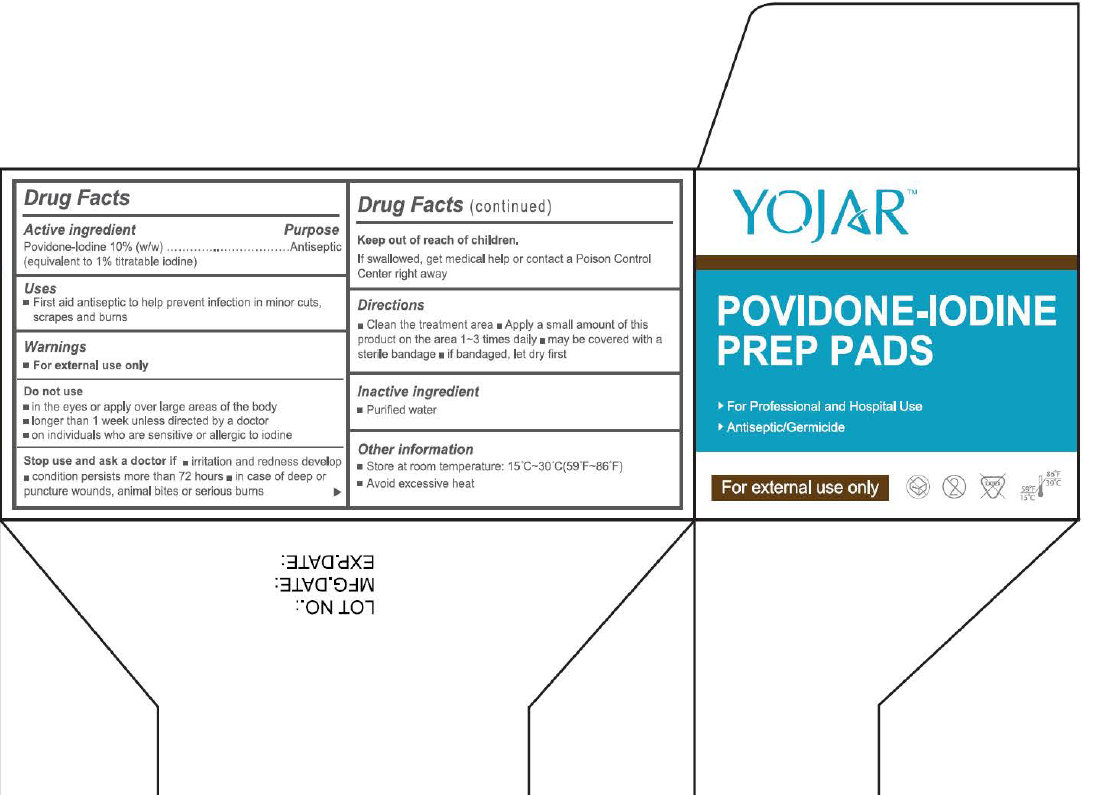 DRUG LABEL: POVIDONE-IODINE PREP
NDC: 44019-100 | Form: PATCH
Manufacturer: Yinjing Medical Technology (Shanghai) Co., Ltd.
Category: otc | Type: HUMAN OTC DRUG LABEL
Date: 20171228

ACTIVE INGREDIENTS: POVIDONE-IODINE 10 g/100 g
INACTIVE INGREDIENTS: WATER

POVIDONE-IODINE PREP

Active ingredient

Povidon-Iodin 10% (w/w)

(equivalent to 1% titratable iodine)

Purpose

Antiseptic

Uses

- First aid antiseptic to help prevent infection in minor cuts, scrapes and burns

Warnings

- For external use only

Do not use

- in the eyes or apply over large areas of the body
- longer than 1 week unless directed by a doctor
- on individuals who are sensitive or allergic to iodine

Stop use and ask a doctor if

- irritation and redness develop
- condition persists more than 72 hours
- in case of deep or puncture wounds, animal bites or serious burns

Keep out of reach of children.

If swallowed, get medical help or contact a Poison Control Center right away

Directions

- Clean the treatment area
- Apply a small amount of this product on the area 1~3 times daily
- may be covered with a sterile bandage
- if bandaged, let dry first

Inactive ingredient

- Purified water

Other information

- Store at room temperature: 15°C~30°C(59°F~86°F)
- Avoid excessive heat